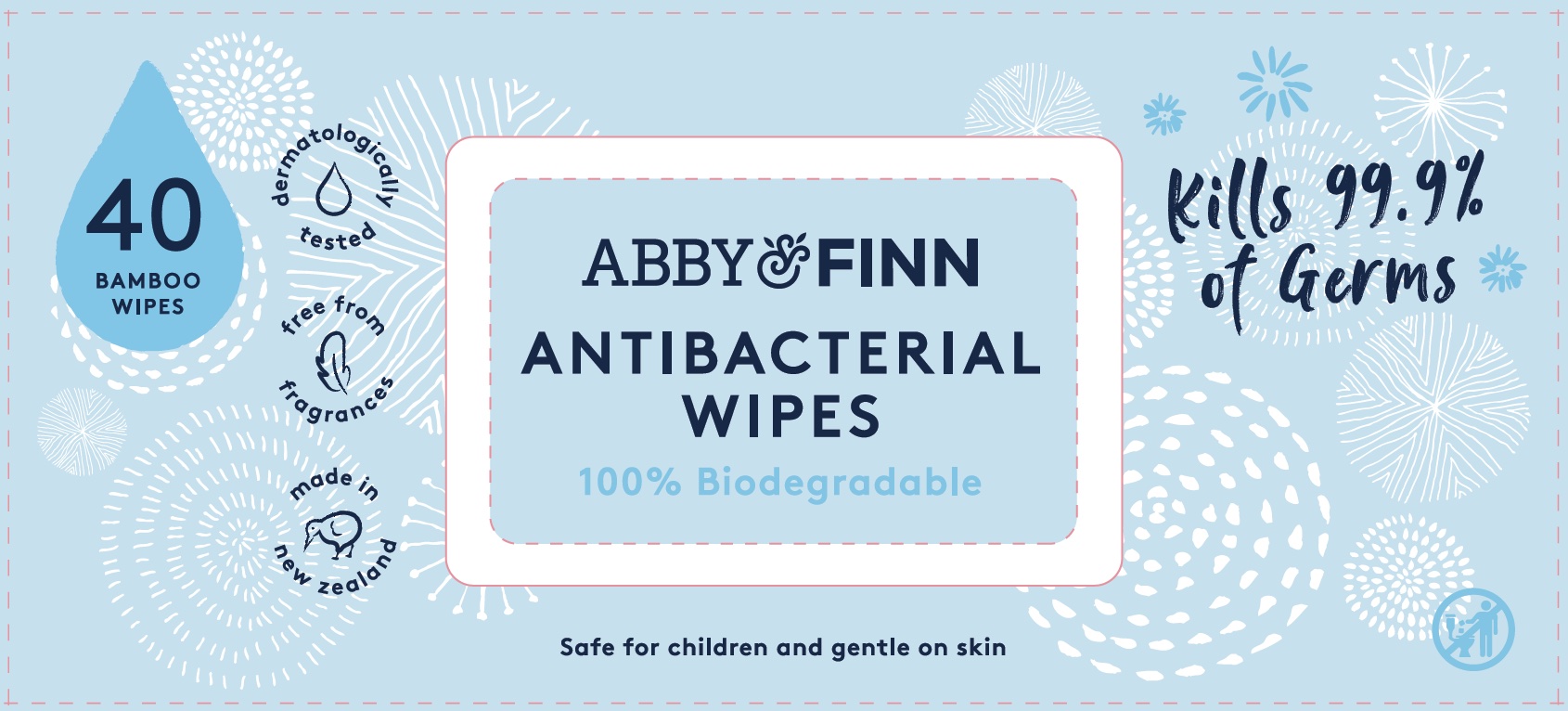 DRUG LABEL: Antibacterial Wipes
NDC: 80202-311 | Form: CLOTH
Manufacturer: Abby&Finn LLC
Category: otc | Type: HUMAN OTC DRUG LABEL
Date: 20210203

ACTIVE INGREDIENTS: BENZALKONIUM CHLORIDE 0.008 g/8.1 g; DIDECYLDIMONIUM CHLORIDE 0.04 g/8.1 g
INACTIVE INGREDIENTS: AMINO ACIDS, SOY; PHENOXYETHANOL; WATER; ISOPROPYL ALCOHOL; BRONOPOL

Abby and Finn Antibacterial Wipes

Active Ingredient(s)

Didecyl Dimethyl Ammonium Chloride 0.5%

Benzalkonium Chloride 0.1%

Purpose

Antibacterial

Antibacterial

Uses

For hand sanitizing to decrease bacteria on the skin.

Do not use

- In the eyes
- If you are allergic to any of the ingredients.

When using this product if eye contact occurs, rinse eyes thoroughly with water.

Stop use and ask a doctor if irritation and redness develop and persist for more than 72 hours.

Keep out of reach of children. If swallowed, get medical help or contact a Poison Control Center right away.

Directions

- Storage. Store at room temperature.
- Dispensing. Peel resealable label back slowly. Reseal after use to avoid wipes drying out.
- Use. Apply wipe thoroughly to hands as desired. Allow to dry without wiping. To ensure best quality, use within 30 days of opening.
- Disposal. Dispose of used wipes in trash receptacle. Do not flush.

Inactive ingredients

Ion Exchanged Water (Food Grade), Propan-2-ol, Bronopol, Natural Soybean Amino Acid (Food Grade), Phenoxyethanol.

Package Label - Principal Display Panel

40 Wipes